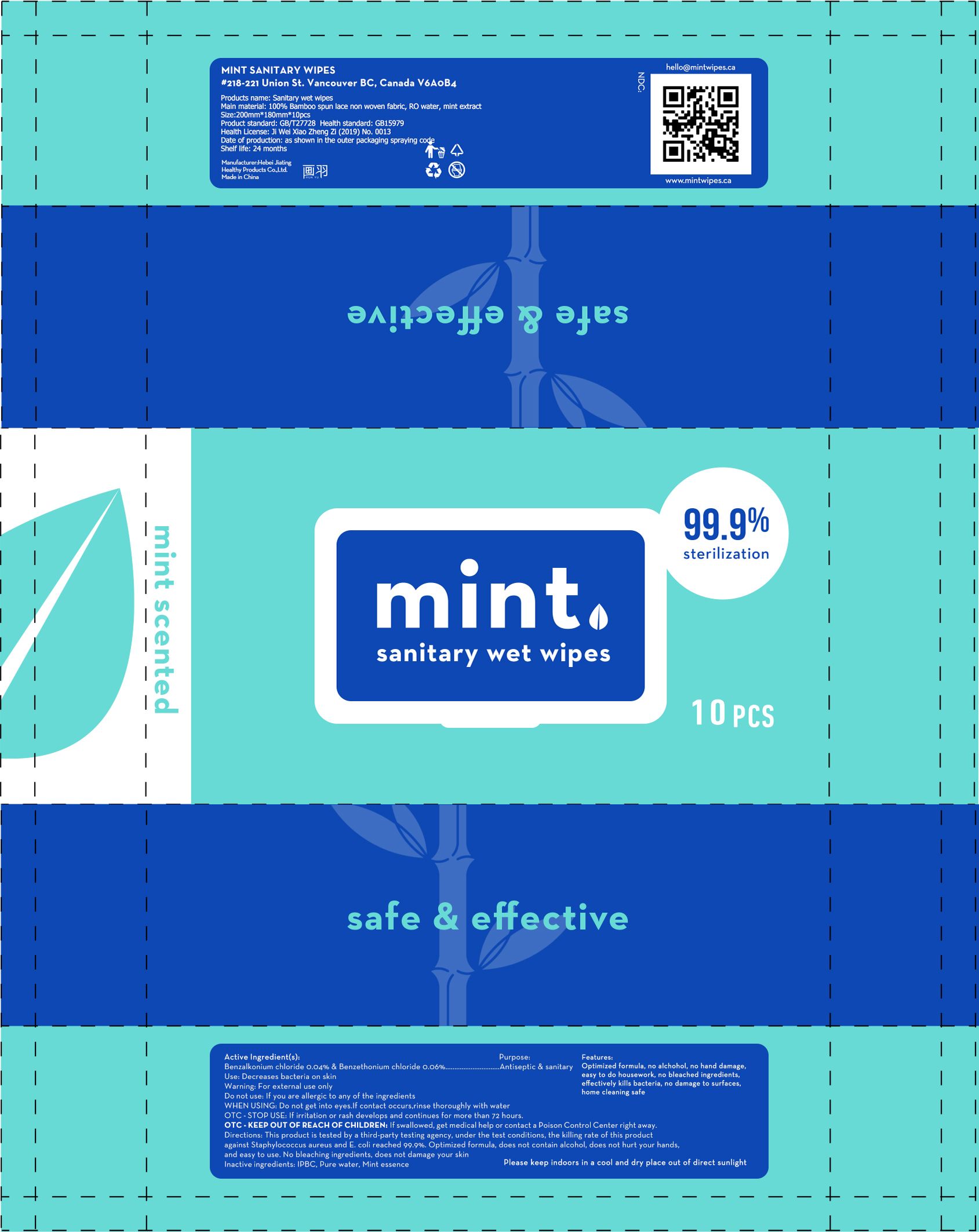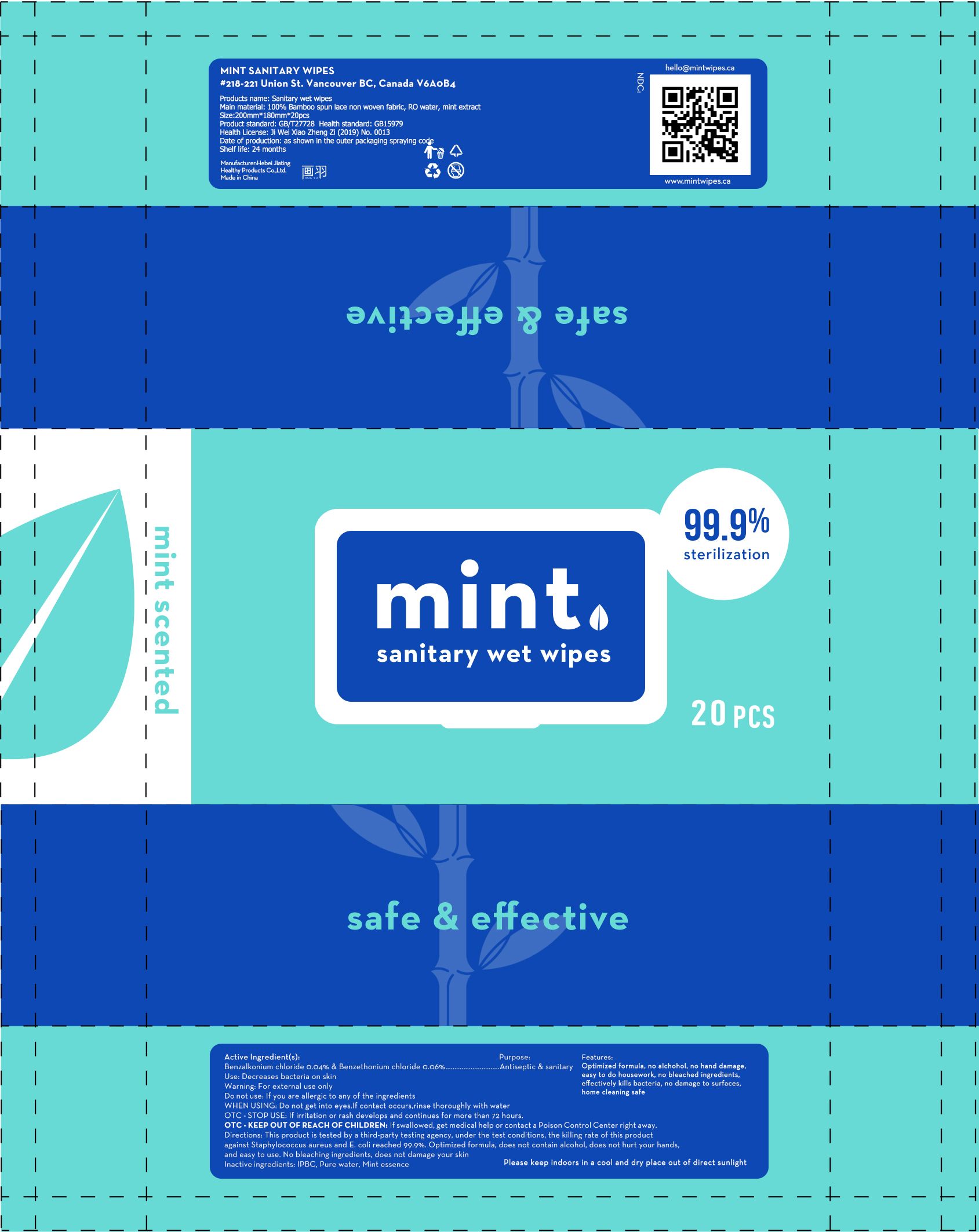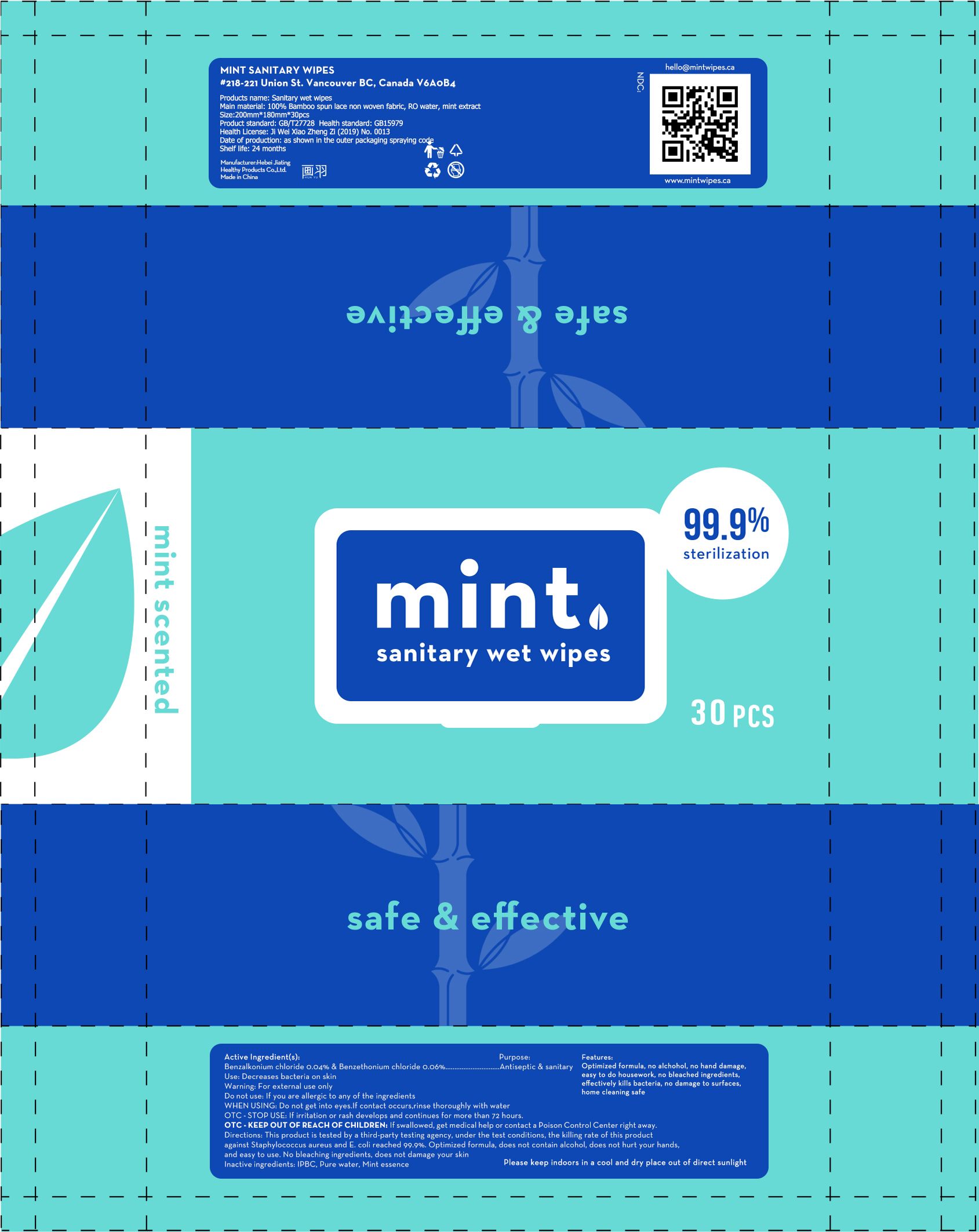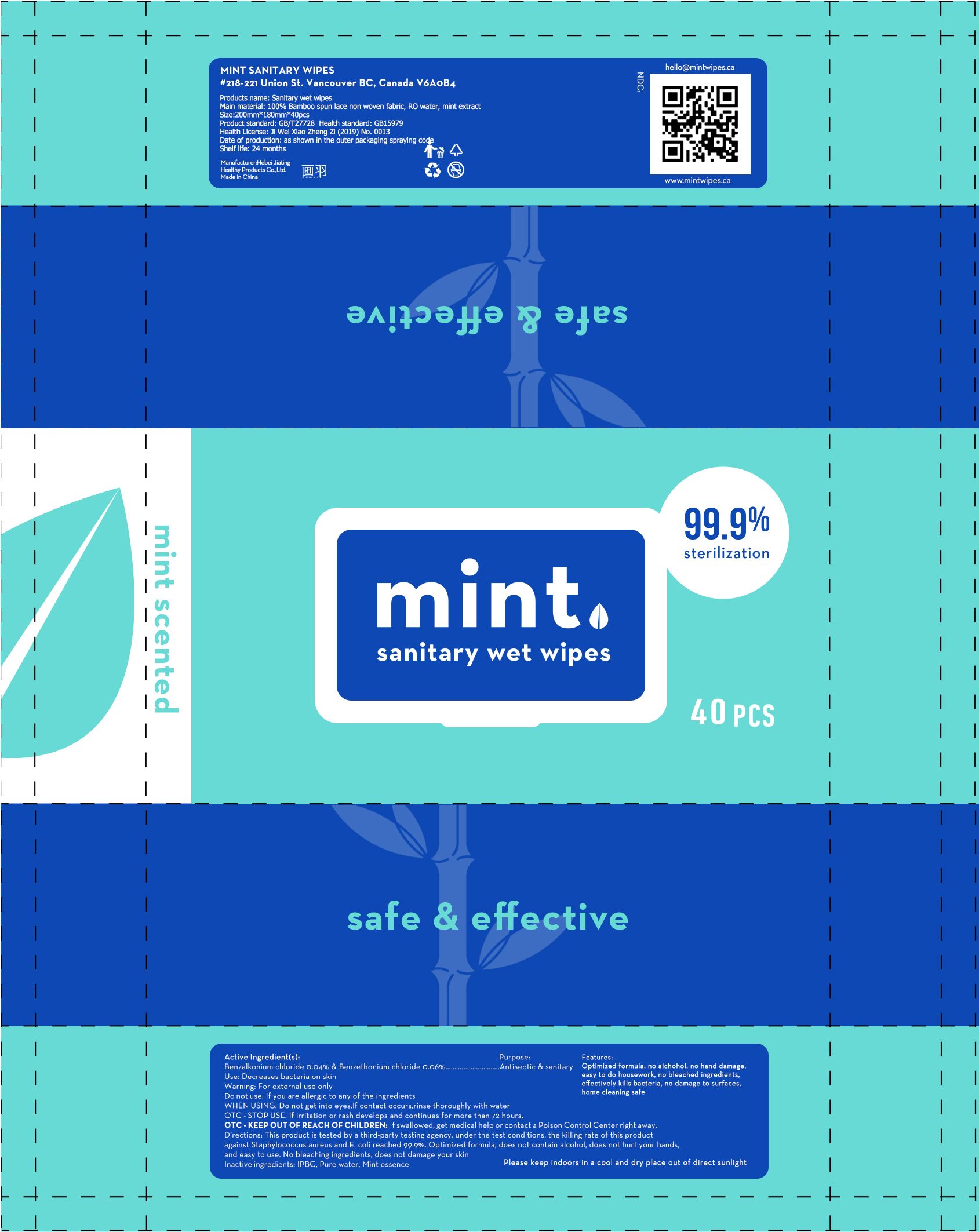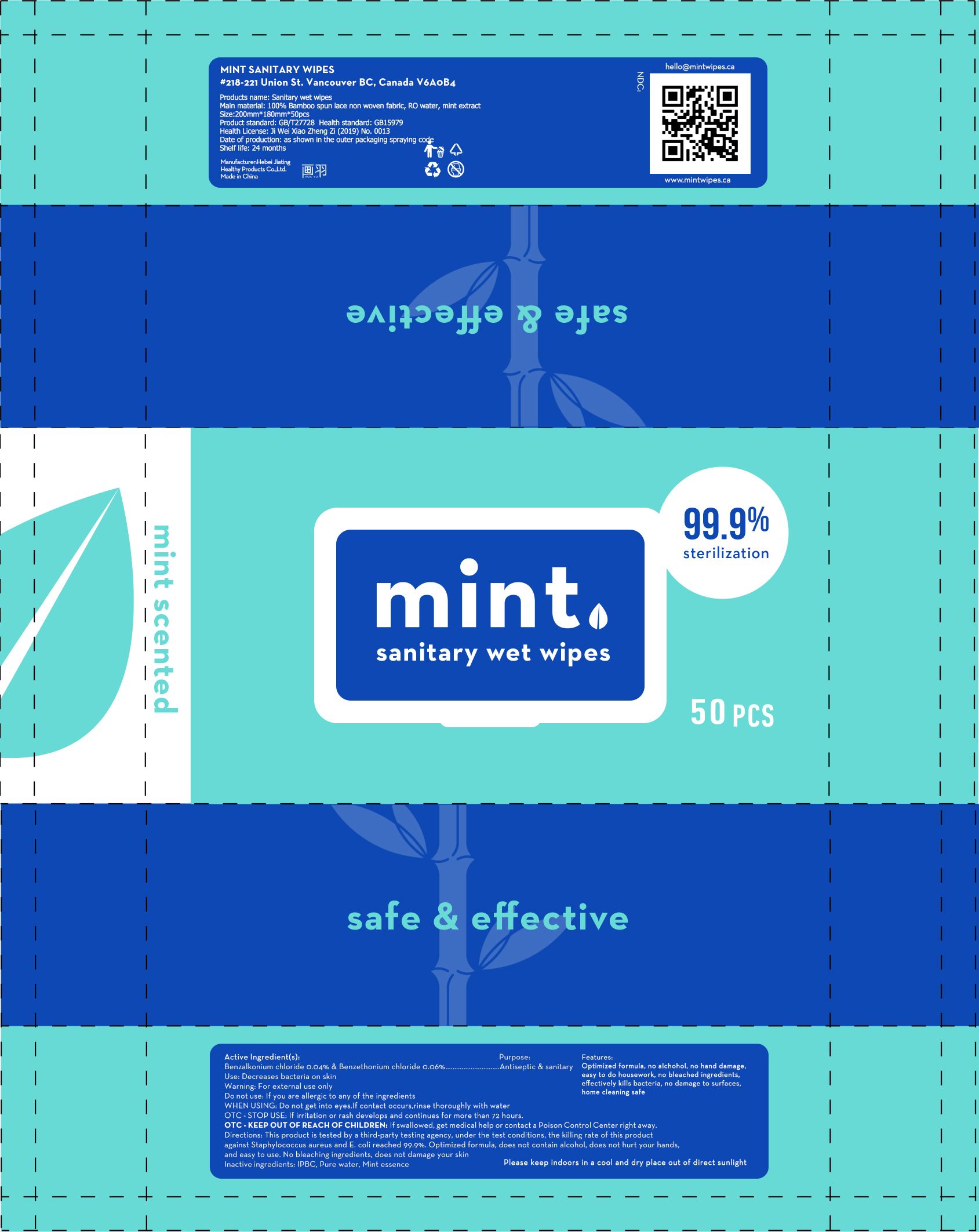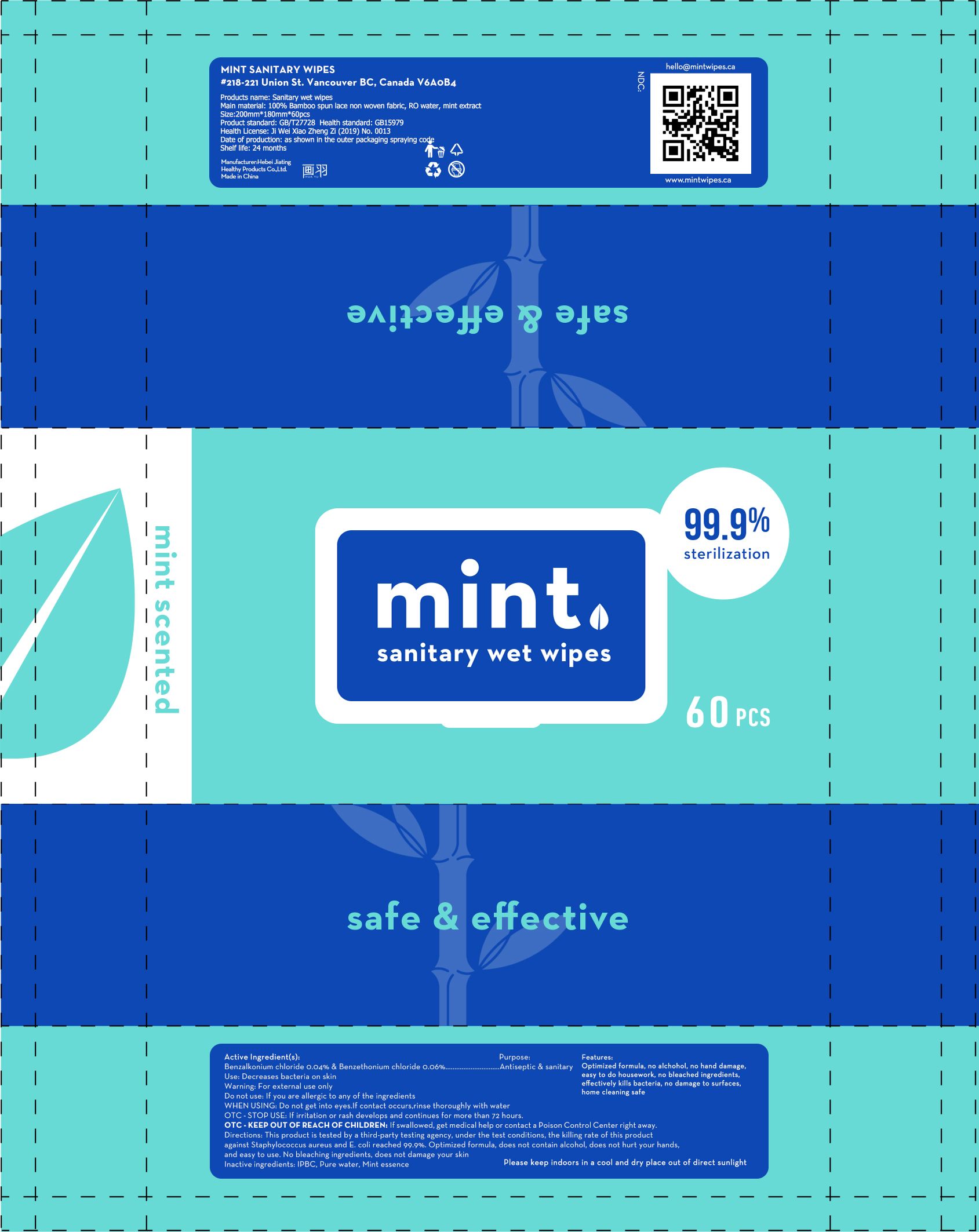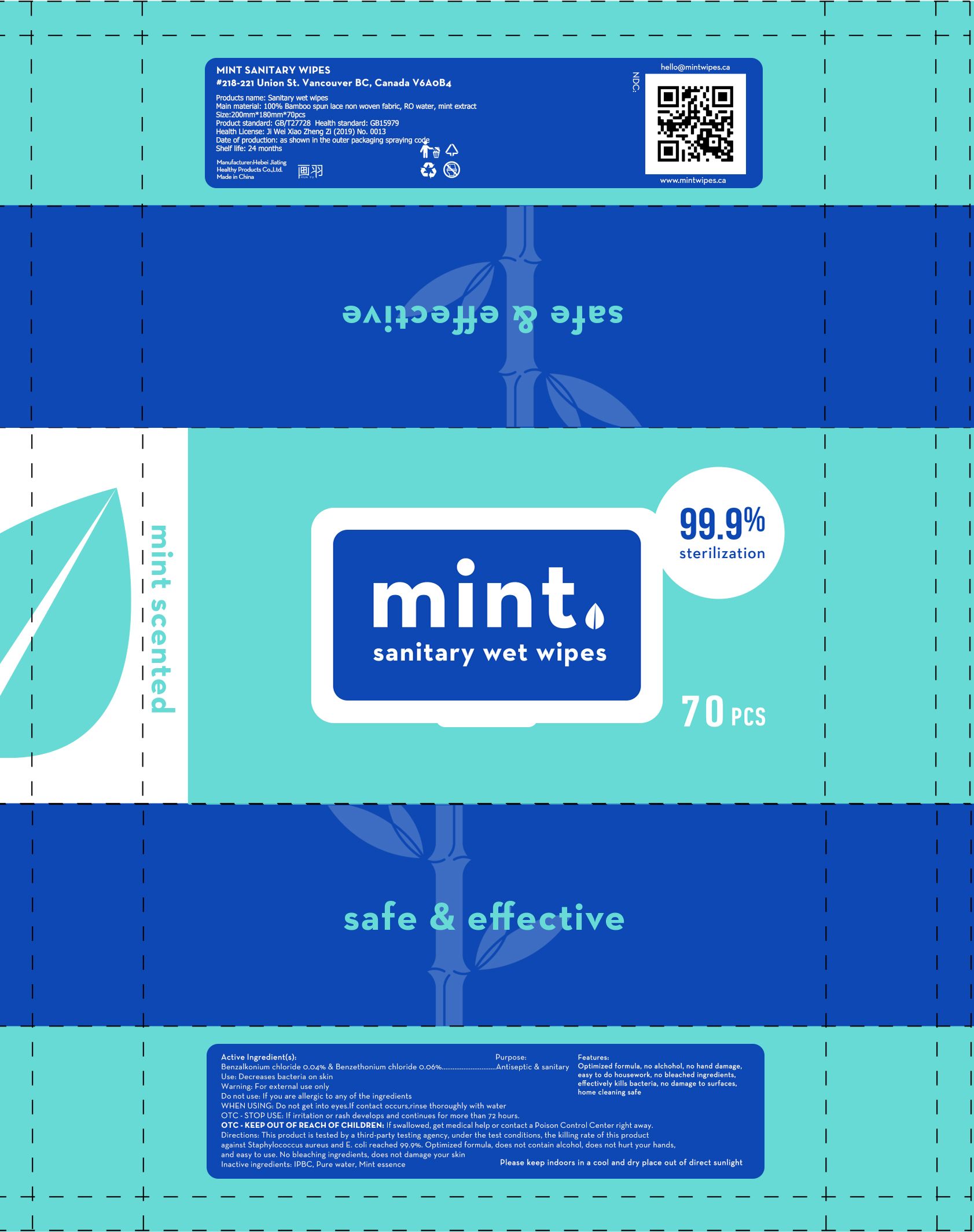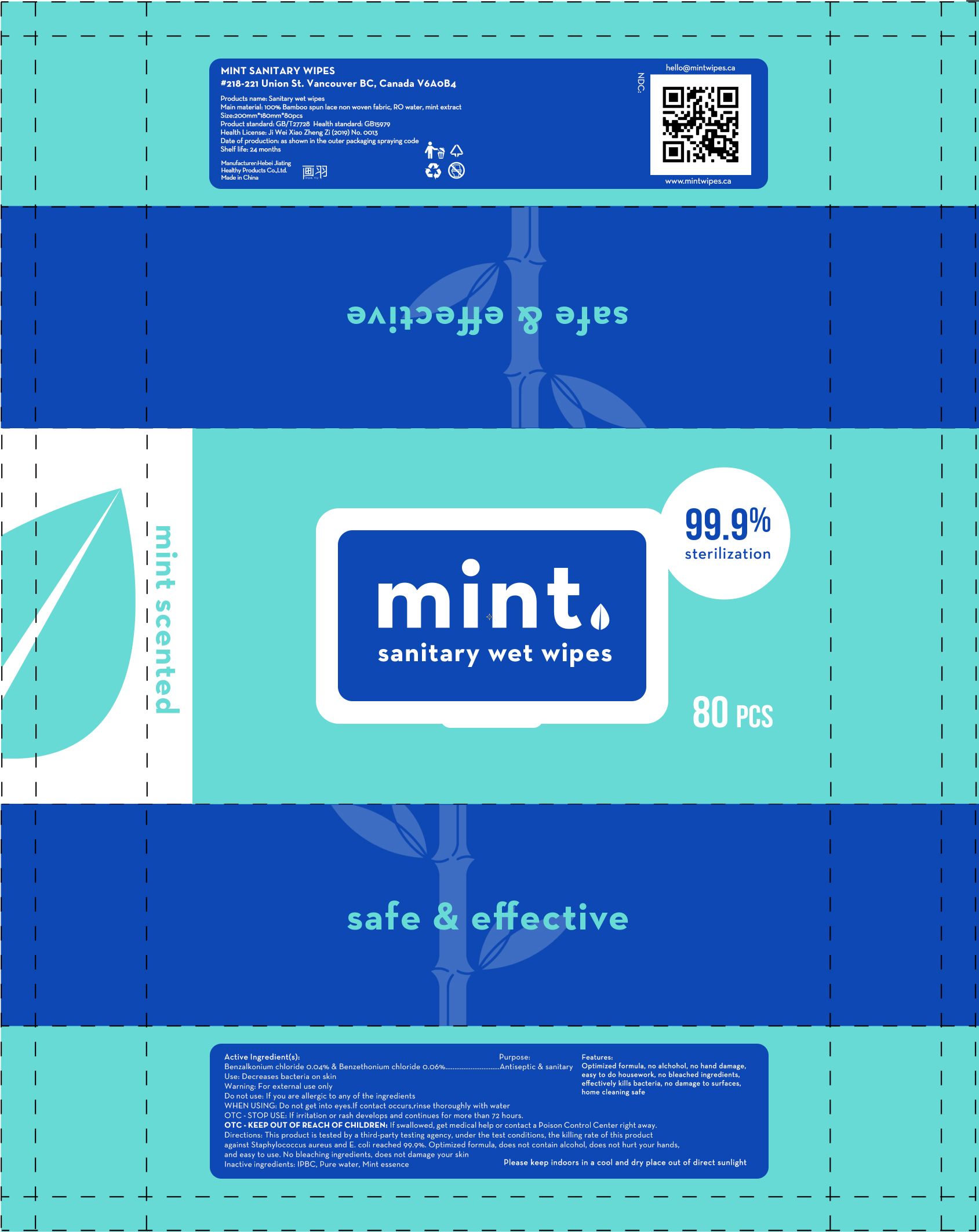 DRUG LABEL: sanitary wet wipes
NDC: 80768-002 | Form: CLOTH
Manufacturer: HEBEI JIATING HEALTH PRODUCT CO.,LTD
Category: otc | Type: HUMAN OTC DRUG LABEL
Date: 20201014

ACTIVE INGREDIENTS: BENZETHONIUM CHLORIDE 0.06 g/100 1; BENZALKONIUM CHLORIDE 0.04 g/100 1
INACTIVE INGREDIENTS: IODOPROPYNYL BUTYLCARBAMATE; MINT; WATER

80768-002
sanitary wet wipes

Active Ingredient(s)

Benzalkonium chloride 0.04%

Benzethonium chloride 0.06%

Purpose

Antiseptic & sanitary

Use

Decreases bacteria on skin

Warnings

For external use only.

Do not use:
If you are allergic to any of the ingredients

When Using:
Do not get into eyes.If contact occurs.rinse thoroughly with water

O T C - Stop Use:
If irritation or rash develops and continues for more than 72 hours

O T C - K E E P O U T O F REACI-I O F CI-IILDREN
If swallowed, get medical help or contact a Poison Control Center right away

Do not use

If you are allergic to any of the ingredients

WHEN USING

Do not get into eyes.If contact occurs.rinse thoroughly with water

O T C - Stop Use:
If irritation or rash develops and continues for more than 72 hours

O T C - K E E P O U T O F REACI-I O F CI-IILDREN
If swallowed, get medical help or contact a Poison Control Center right away

STOP USE

If irritation or rash develops and continues for more than 72 hours

KEEP OUT OF REACH OF CHILDREN

If swallowed, get medical help or contact a Poison Control Center right away

Directions

This product is tested by a third-party testing agency under the test conditions, the killing rate of thrs product against Slaphylococc1.1s aureus and oli readied 99.9% . Optimized formula . does not ontain alcohol. does not hurt your 1-iands, and easy to use. No bleaching ingredients. cloes not damage your skfn

Other information

/

Inactive ingredients

IPBC, Pure water, Mint essence